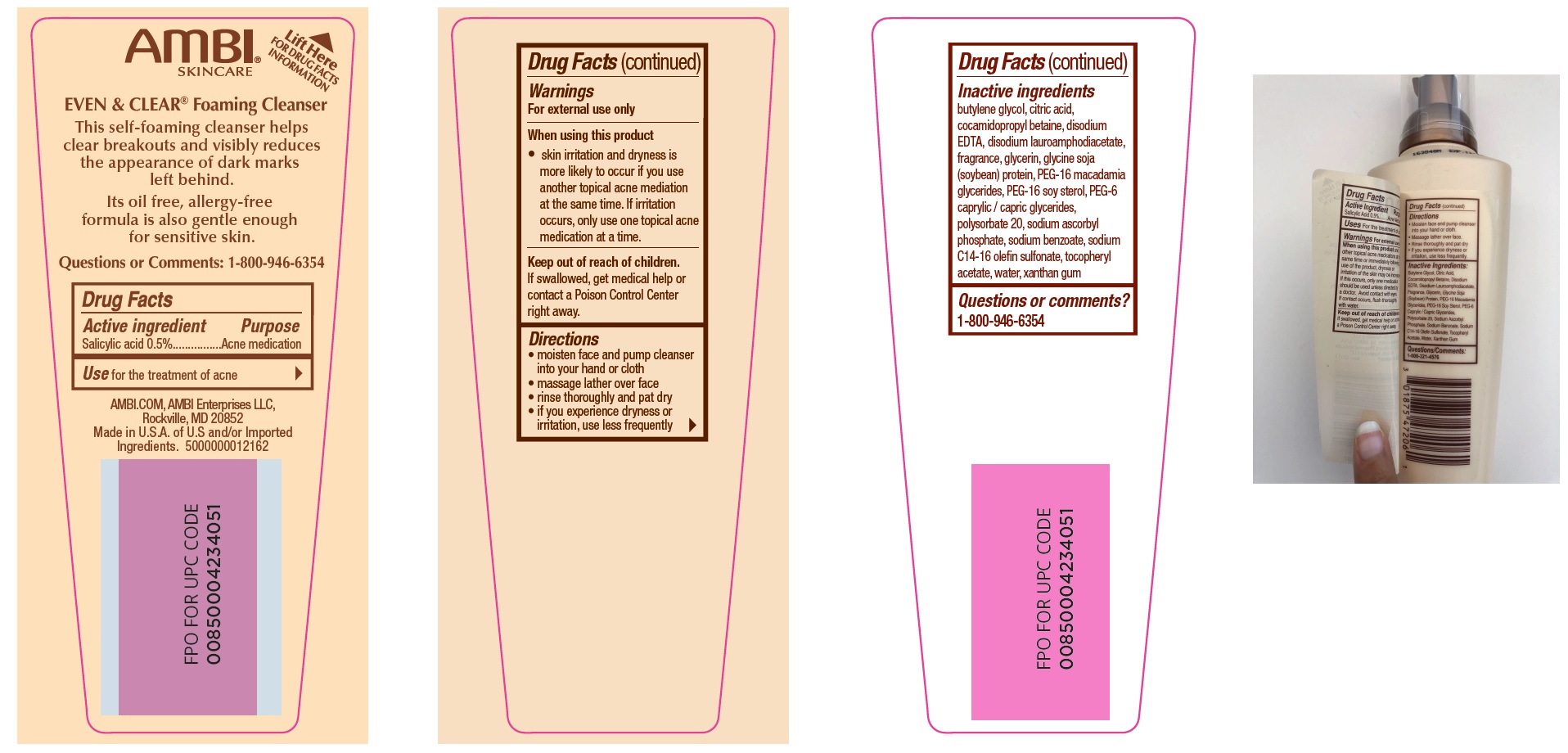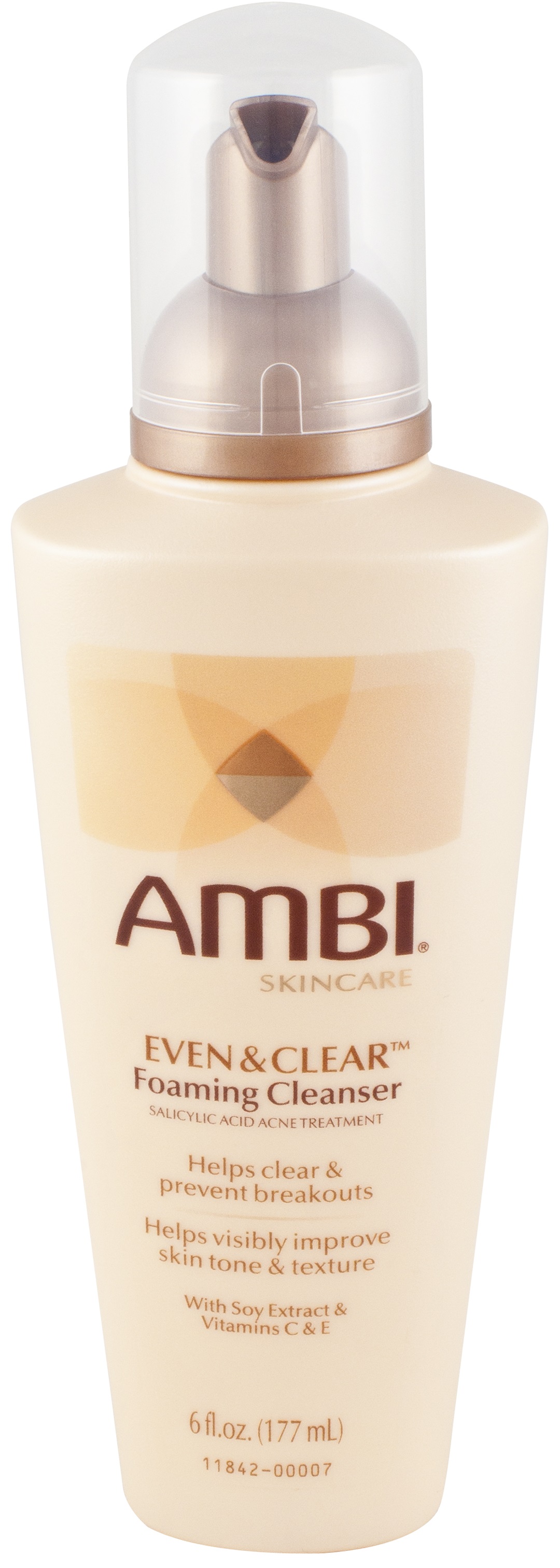 DRUG LABEL: Even and Clear Cleanser
NDC: 73453-003 | Form: LIQUID
Manufacturer: Ambi Enterprises LLC
Category: otc | Type: HUMAN OTC DRUG LABEL
Date: 20250724

ACTIVE INGREDIENTS: SALICYLIC ACID 5 mg/1 mL
INACTIVE INGREDIENTS: XANTHAN GUM; BUTYLENE GLYCOL; CITRIC ACID MONOHYDRATE; EDETATE DISODIUM ANHYDROUS; DISODIUM LAUROAMPHODIACETATE; GLYCERIN; SOYBEAN; PEG-16 MACADAMIA GLYCERIDES; PEG-16 SOY STEROL; PEG-6 CAPRYLIC/CAPRIC GLYCERIDES; POLYSORBATE 20; SODIUM ASCORBYL PHOSPHATE; SODIUM BENZOATE; SODIUM C14-16 OLEFIN SULFONATE; .ALPHA.-TOCOPHEROL ACETATE; WATER

Even & Clear Foaming Cleanser

Active ingredient

Salicylic acid 0.5%

Purpose

Acne medication

Use

for the treatment of acne

Warnings

For external use only

When using this product

- skin irritation and dryness is more likely to occur if you use another topical acne mediation at the same time. If irritation occurs, only use one topical acne medication at a time.

Keep out of reach of children.

If swallowed, get medical help or contact a Poison Control Center right away.

Directions

- moisten face and pump cleanser into your hand or cloth
- massage lather over face
- rinse thoroughly and pat dry
- if you experience dryness or irritation, use less frequently

Inactive ingredients

butylene glycol, citric acid, cocamidopropyl betaine, disodium EDTA, disodium lauroamphodiacetate, fragrance, glycerin, glycine soja (soybean) protein, PEG-16 macadamia glycerides, PEG-16 soy sterol, PEG-6 caprylic / capric glycerides, polysorbate 20, sodium ascorbyl phosphate, sodium benzoate, sodium C14-16 olefin sulfonate, tocopheryl acetate, water, xanthan gum

Questions or comments?

1-800-946-6354